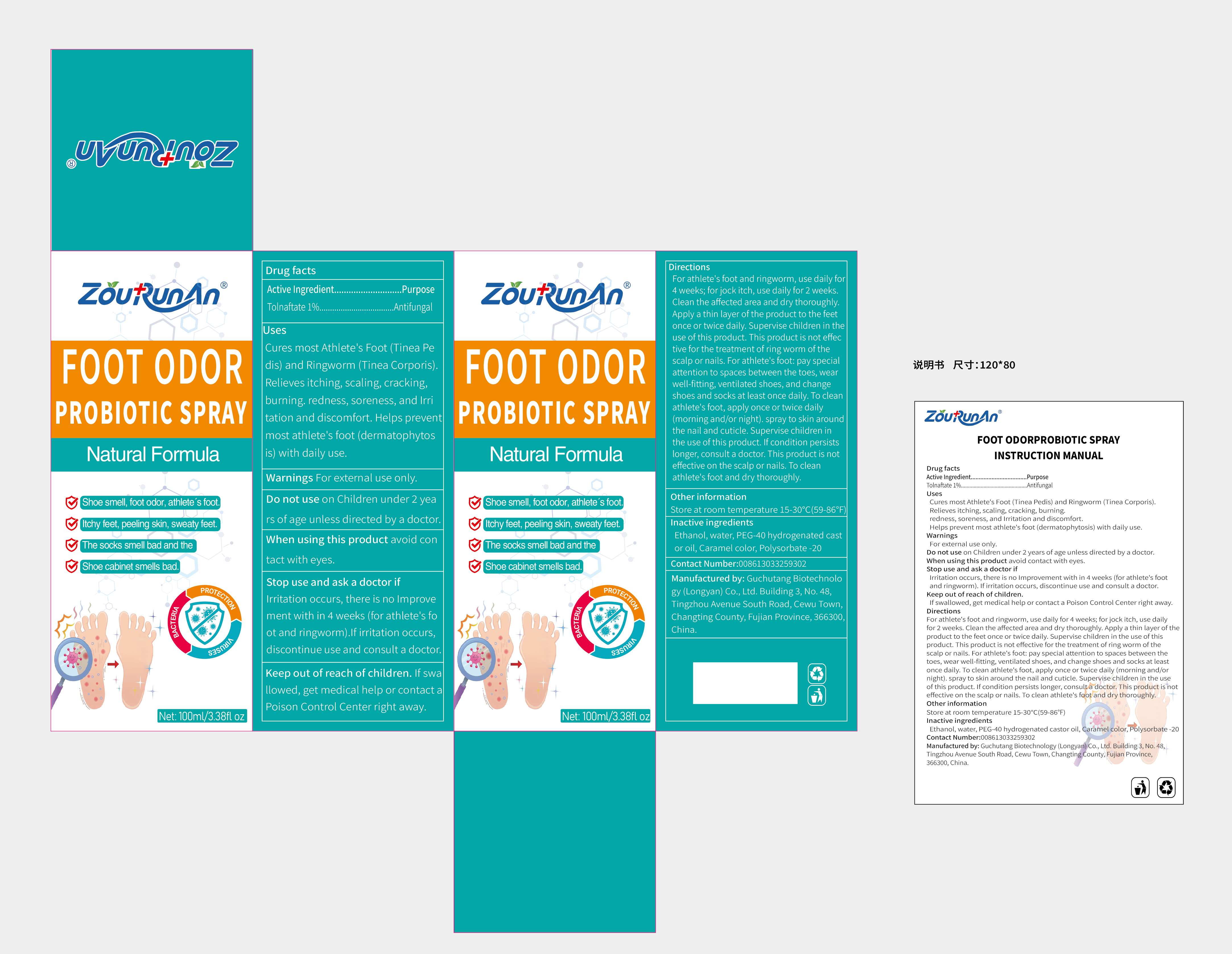 DRUG LABEL: zourunan FOOT ODOR PROBIOTIC
NDC: 87083-004 | Form: SPRAY
Manufacturer: Guchutang Biotechnology (Longyan) Co., Ltd
Category: otc | Type: HUMAN OTC DRUG LABEL
Date: 20251022

ACTIVE INGREDIENTS: TOLNAFTATE 1 g/100 mL
INACTIVE INGREDIENTS: ALCOHOL; POLYSORBATE 20; POLYOXYL 40 HYDROGENATED CASTOR OIL; CARAMEL; WATER

87083-004

Active Ingredient

Tolnaftate 1%

Purpose

Antifungal

Use

Cures most Athlete's Foot (Tinea Pedis) and Ringworm (Tinea Corporis). Relieves itching, scaling, cracking, burning. redness, soreness, and Irri tation and discomfort.Helps prevent most athlete's foot (dermatophytos is) with daily use.

Warnings

For external use only.

Do not use on Children under 2 years of age unless directed by a doctor.

When Using

When using this product avoid contact with eyes.

Stop Use

Irritation occurs, there is no Improvement with in 4 weeks (for athlete's foot and ringworm).If irritation occurs, discontinue use and consult a doctor.

Ask Doctor

If irritation occurs, discontinue use and consult a doctor.

Keep Out Of Reach Of Children

If swallowed, get medical help or contact a Poison Control Center right away.

Directions

For athlete's foot and ringworm, use daily for 4 weeks; for jock itch, use daily for 2 weeks.

Clean the affected area and dry thoroughly. Apply a thin layer of the product to the feet once or twice daily.Supervise child ren in the

use of this product. This product is not effective for the treatment of ring worm of the

scalp or nails. For athlete's foot: pay special attention to spaces between the toes, wear well-fitting, ventilated shoes, and change shoes and socks at least once daily.

To clean athlete's foot, apply once or twice daily (morning and/or night). Apply to skin aroundthe nail and cuticle.Supervise children in the use of this product. If condition persists longer, consult a doctor. This product is not effective on the scalp or nails. To clean athlete's foot the feet and dry thoroughly.

Other information

Store at room temperature 15-30℃(59-86℉)

Inactive ingredients

Ethanol, water, PEG-40 hydrogenated castor oil Caramel color, Polysorbate -20